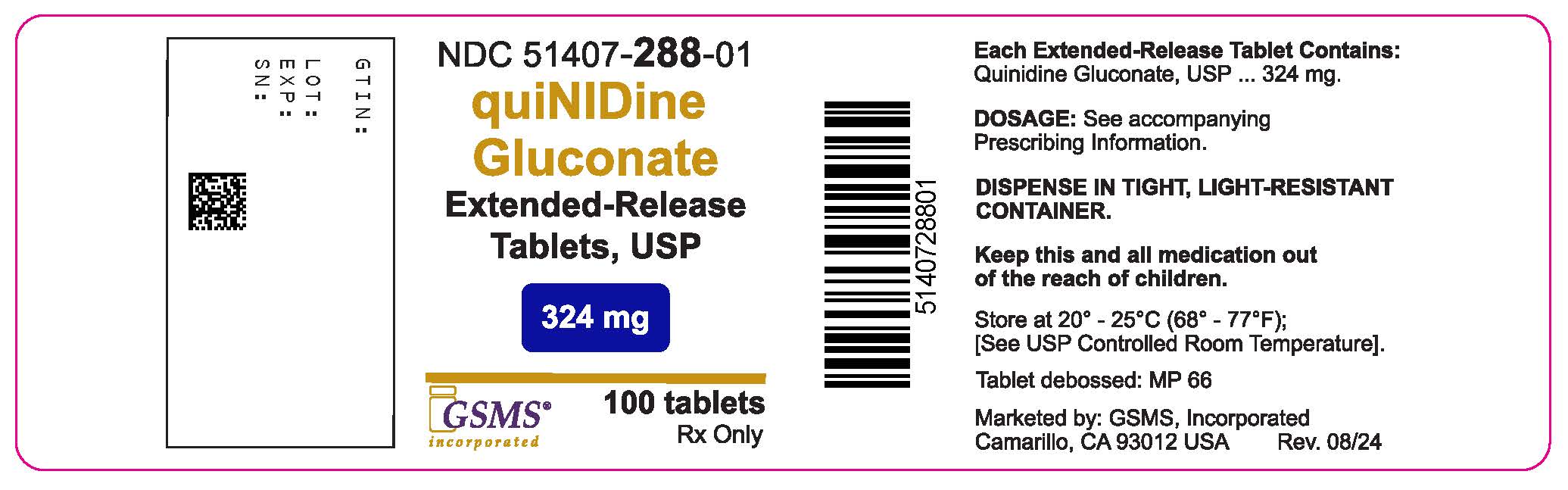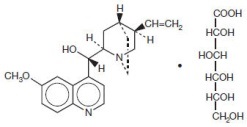 DRUG LABEL: Quinidine Gluconate
NDC: 51407-288 | Form: TABLET, EXTENDED RELEASE
Manufacturer: Golden State Medical Supply
Category: prescription | Type: HUMAN PRESCRIPTION DRUG LABEL
Date: 20240827

ACTIVE INGREDIENTS: QUINIDINE GLUCONATE 324 mg/1 1

QUINIDINE GLUCONATE
EXTENDED-RELEASE TABLETS USP

Rx only

DESCRIPTION

Quinidine is an antimalarial schizonticide and an antiarrhythmic agent with Class Ia activity; it is the d-isomer of quinine, and its molecular weight is 324.43. Quinidine gluconate is the gluconate salt of quinidine; its chemical name is cinchonan-9-ol, 6'-methoxy-, (9S)-, mono-D-gluconate; its structural formula is:

Its empirical formula is C20H24N2O2 • C6H12O7, and its molecular weight is 520.58, of which 62.3% is quinidine base.

Each quinidine gluconate extended-release tablet contains 324 mg of quinidine gluconate (202 mg of quinidine base) in a matrix to provide extended-release; the inactive ingredients include corn starch, hydroxypropyl methylcellulose, magnesium stearate, microcrystalline cellulose, povidone, silicon dioxide, and sodium alginate.

This product complies with USP Drug Release Test 5.

CLINICAL PHARMACOLOGY

Pharmacokinetics and Metabolism

The absolute bioavailability of quinidine from quinidine gluconate is 70 to 80%. Relative to a solution of quinidine sulfate, the bioavailability of quinidine from quinidine gluconate is reported to be 1.03. The less-than-complete bioavailability is thought to be due to first-pass elimination by the liver. Peak serum levels generally appear 3 to 5 hours after dosing; when the drug is taken with food, absorption is increased in both rate (27%) and extent (17%). The rate and extent of absorption of quinidine from quinidine gluconate are not significantly affected by the coadministration of an aluminum-hydroxide antacid. The rate of absorption of quinidine following the ingestion of grapefruit juice may be decreased.

The volume of distribution of quinidine is 2 to 3 L/kg in healthy young adults, but this may be reduced to as little as 0.5 L/kg in patients with congestive heart failure, or increased to 3 to 5 L/kg in patients with cirrhosis of the liver. At concentrations of 2 to 5 mg/L (6.5 to 16.2 µmol/L), the fraction of quinidine bound to plasma proteins (mainly to α1-acid glycoprotein and to albumin) is 80 to 88% in adults and older children, but it is lower in pregnant women, and in infants and neonates it may be as low as 50 to 70%. Because α1-acid glycoprotein levels are increased in response to stress, serum levels of total quinidine may be greatly increased in settings such as acute myocardial infarction, even though the serum content of unbound (active) drug may remain normal. Protein binding is also increased in chronic renal failure, but binding abruptly descends toward or below normal when heparin is administered for hemodialysis.

Quinidine clearance typically proceeds at 3 to 5 mL/min/kg in adults, but clearance in children may be twice or three times as rapid. The elimination half-life is 6 to 8 hours in adults and 3 to 4 hours in children. Quinidine clearance is unaffected by hepatic cirrhosis, so the increased volume of distribution seen in cirrhosis leads to a proportionate increase in the elimination half-life.

Most quinidine is eliminated hepatically via the action of cytochrome P450IIIA4; there are several different hydroxylated metabolites, and some of these have antiarrhythmic activity.

The most important of quinidine's metabolites is 3-hydroxy-quinidine (3HQ), serum levels of which can approach those of quinidine in patients receiving conventional doses of quinidine gluconate. The volume of distribution of 3HQ appears to be larger than that of quinidine, and the elimination half-life of 3HQ is about 12 hours.

As measured by antiarrhythmic effects on animals, by QTc prolongation in human volunteers, or by various in vitro techniques, 3HQ has at least half the antiarrhythmic activity of the parent compound, so it may be responsible for a substantial fraction of the effect of quinidine gluconate in chronic use.

When the urine pH is less than 7, about 20% of administered quinidine appears unchanged in the urine, but this fraction drops to as little as 5% when the urine is more alkaline. Renal clearance involves both glomerular filtration and active tubular secretion, moderated by (pH-dependent) tubular reabsorption. The net renal clearance is about 1 mL/min/kg in healthy adults. When renal function is taken into account, quinidine clearance is apparently independent of patient age.

Assays of serum quinidine levels are widely available, but the results of modern assays may not be consistent with results cited in the older medical literature. The serum levels of quinidine cited in this package insert are those derived from specific assays, using either benzene extraction or (preferably) reverse-phase high-pressure liquid chromatography. In matched samples, older assays might unpredictably have given results that were as much as two or three times higher. A typical "therapeutic" concentration range is 2 to 6 mg/L (6.2 to 18.5 µmol/L).

Mechanisms of action

In patients with malaria, quinidine acts primarily as an intra-erythrocytic schizonticide, with little effect upon sporozites or upon pre-erythrocytic parasites. Quinidine is gametocidal to Plasmodium vivax and P. malariae, but not to P. falciparum.

In cardiac muscle and in Purkinje fibers, quinidine depresses the rapid inward depolarizing sodium current, thereby slowing phase-0 depolarization and reducing the amplitude of the action potential without affecting the resting potential. In normal Purkinje fibers, it reduces the slope of phase-4 depolarization, shifting the threshold voltage upward toward zero. The result is slowed conduction and reduced automaticity in all parts of the heart, with increase of the effective refractory period relative to the duration of the action potential in the atria, ventricles, and Purkinje tissues. Quinidine also raises the fibrillation thresholds of the atria and ventricles, and it raises the ventricular defibrillation threshold as well. Quinidine's actions fall into Class Ia in the Vaughn-Williams classification.

By slowing conduction and prolonging the effective refractory period, quinidine can interrupt or prevent reentrant arrhythmias and arrhythmias due to increased automaticity, including atrial flutter, atrial fibrillation, and paroxysmal supraventricular tachycardia.

In patients with sick sinus syndrome, quinidine can cause marked sinus node depression and bradycardia. In most patients, however, use of quinidine is associated with an increase in the sinus rate.

Like other antiarrhythmic drugs with Class Ia activity, quinidine prolongs the QT interval in a dose-related fashion. This may lead to increased ventricular automaticity and polymorphic ventricular tachycardias, including torsades de pointes (see WARNINGS).

In addition, quinidine has anticholinergic activity, it has negative inotropic activity, and it acts peripherally as an α-adrenergic antagonist (that is, as a vasodilator).

Clinical Effects

Maintenance of sinus rhythm after conversion from atrial fibrillation: In six clinical trials (published between 1970 and 1984) with a total of 808 patients, quinidine (418 patients) was compared to nontreatment (258 patients) or placebo (132 patients) for the maintenance of sinus rhythm after cardioversion from chronic atrial fibrillation. Quinidine was consistently more efficacious in maintaining sinus rhythm, but a meta-analysis found that mortality in the quinidine-exposed patients (2.9%) was significantly greater than mortality in the patients who had not been treated with active drug (0.8%). Suppression of atrial fibrillation with quinidine has theoretical patient benefits (e.g., improved exercise tolerance; reduction in hospitalization for cardioversion; lack of arrhythmia-related palpitations, dyspnea and chest pain; reduced incidence of systemic embolism and/or stroke), but these benefits have never been demonstrated in clinical trials. Some of these benefits (e.g., reduction in stroke incidence) may be achievable by other means (anticoagulation).

By slowing the atrial rate in atrial flutter/fibrillation, quinidine can decrease the degree of atrioventricular block and cause an increase, sometimes marked, in the rate at which supraventricular impulses are successfully conducted by the atrioventricular node, with a resultant paradoxical increase in ventricular rate (see WARNINGS).

Non-life-threatening ventricular arrhythmias: In studies of patients with a variety of ventricular arrhythmias (mainly frequent ventricular premature beats and non-sustained ventricular tachycardia, quinidine (total n=502) has been compared with flecainide (n=141), mexiletine (n=246), propafenone (n=53), and tocainide (n=67). In each of these studies, the mortality in the quinidine group was numerically greater than the mortality in the comparator group. When the studies were combined in a meta-analysis, quinidine was associated with a statistically significant threefold relative risk of death.

At therapeutic doses, quinidine's only consistent effect upon the surface electrocardiogram is an increase in the QT interval. This prolongation can be monitored as a guide to safety, and it may provide better guidance than serum drug levels (see WARNINGS).

INDICATIONS AND USAGE

Conversion of atrial fibrillation/flutter

In patients with symptomatic atrial fibrillation/flutter whose symptoms are not adequately controlled by measures that reduce the rate of ventricular response, quinidine gluconate is indicated as a means of restoring normal sinus rhythm. If this use of quinidine gluconate does not restore sinus rhythm within a reasonable time (see DOSAGE AND ADMINISTRATION), then quinidine gluconate should be discontinued.

Reduction of frequency of relapse into atrial fibrillation/flutter

Chronic therapy with quinidine gluconate is indicated for some patients at high risk of symptomatic atrial fibrillation/flutter, generally patients who have had previous episodes of atrial fibrillation/flutter that were so frequent and poorly tolerated as to outweigh, in the judgment of the physician and the patient, the risks of prophylactic therapy with quinidine gluconate. The increased risk of death should specifically be considered. Quinidine gluconate should be used only after alternative measures (e.g., use of other drugs to control the ventricular rate) have been found to be inadequate.

In patients with histories of frequent symptomatic episodes of atrial fibrillation/flutter, the goal of therapy should be an increase in the average time between episodes. In most patients, the tachyarrhythmia will recur during therapy, and a single recurrence should not be interpreted as therapeutic failure.

Suppression of ventricular arrhythmias

Quinidine gluconate is also indicated for the suppression of recurrent documented ventricular arrhythmias, such as sustained ventricular tachycardia, that in the judgment of the physician are life-threatening. Because of the proarrhythmic effects of quinidine, its use with ventricular arrhythmias of lesser severity is generally not recommended, and treatment of patients with asymptomatic ventricular premature contractions should be avoided. Where possible, therapy should be guided by the results of programmed electrical stimulation and/or Holter monitoring with exercise.

Antiarrhythmic drugs (including quinidine gluconate) have not been shown to enhance survival in patients with ventricular arrhythmias.

CONTRAINDICATIONS

Quinidine is contraindicated in patients who are known to be allergic to it, or who have a history of immune thrombocytopenia or have developed thrombocytopenic purpura during prior therapy with quinidine or quinine (see WARNINGS).

In the absence of a functioning artificial pacemaker, quinidine is also contraindicated in any patient whose cardiac rhythm is dependent upon a junctional or idioventricular pacemaker, including patients in complete atrioventricular block.

Quinidine is also contraindicated in patients who, like those with myasthenia gravis, might be adversely affected by an anticholinergic agent.

WARNINGS

Mortality:

BOXED WARNING

In many trials of antiarrhythmic therapy for non-life-threatening arrhythmias, active antiarrhythmic therapy has resulted in increased mortality; the risk of active therapy is probably greatest in patients with structural heart disease.

In the case of quinidine used to prevent or defer recurrence of atrial flutter/fibrillation, the best available data come from a meta-analysis described under CLINICAL PHARMACOLOGY/Clinical Effects above. In the patients studied in the trials there analyzed, the mortality associated with the use of quinidine was more than three times as great as the mortality associated with the use of placebo.

Another meta-analysis, also described under CLINICAL PHARMACOLOGY/Clinical Effects, showed that in patients with various non-life-threatening ventricular arrhythmias, the mortality associated with the use of quinidine was consistently greater than that associated with the use of any of a variety of alternative antiarrhythmics.

Proarrhythmic effects

Like many other drugs (including all other Class Ia antiarrhythmics), quinidine prolongs the QTc interval, and this can lead to torsades de pointes, a life-threatening ventricular arrhythmia (see OVERDOSAGE). The risk of torsades is increased by bradycardia, hypokalemia, hypomagnesemia or high serum levels of quinidine, but it may appear in the absence of any of these risk factors. The best predictor of this arrhythmia appears to be the length of QTc interval, and quinidine should be used with extreme care in patients who have preexisting long-QT syndromes, who have histories of torsades de pointes of any cause, or who have previously responded to quinidine (or other drugs that prolong ventricular repolarization) with marked lengthening of the QTc interval. Estimation of the incidence of torsades in patients with therapeutic levels of quinidine is not possible from the available data.

Other ventricular arrhythmias that have been reported with quinidine include frequent extrasystoles, ventricular tachycardia, ventricular flutter, and ventricular fibrillation.

Paradoxical increase in ventricular rate in atrial flutter/fibrillation

When quinidine is administered to patients with atrial flutter/fibrillation, the desired pharmacologic reversion to sinus rhythm may (rarely) be preceded by a slowing of the atrial rate with a consequent increase in the rate of beats conducted to the ventricles. The resulting ventricular rate may be very high (greater than 200 beats per minute) and poorly tolerated. This hazard may be decreased if partial atrioventricular block is achieved prior to initiation of quinidine therapy, using conduction-reducing drugs such as digitalis, verapamil, diltiazem, or a β-receptor blocking agent.

Exacerbated bradycardia in sick sinus syndrome

In patients with the sick sinus syndrome, quinidine has been associated with marked sinus node depression and bradycardia.

Pharmacokinetic considerations

Renal or hepatic dysfunction causes the elimination of quinidine to be slowed, while congestive heart failure causes a reduction in quinidine's apparent volume of distribution. Any of these conditions can lead to quinidine toxicity if dosage is not appropriately reduced. In addition, interactions with coadministered drugs can alter the serum concentration and activity of quinidine, leading either to toxicity or to lack of efficacy if the dose of quinidine is not appropriately modified (see PRECAUTIONS/Drug Interactions).

Vagolysis

Because quinidine opposes the atrial and A-V nodal effects of vagal stimulation, physical or pharmacological vagal maneuvers undertaken to terminate paroxysmal supraventricular tachycardia may be ineffective in patients receiving quinidine.

Thrombocytopenia

Quinidine-induced thrombocytopenia is an immune-mediated disorder characterized by a drug-dependent antibody that is itself nonreactive, but when soluble drug is present at pharmacologic concentrations, binds tightly to specific platelet membrane glycoproteins, causing platelet destruction.^1 Serologic testing for quinidine-specific antibody is commercially available and may be useful for identifying the specific cause of thrombocytopenia in individual cases. Testing is important because a patient with quinidine-dependent antibodies should not be re-exposed to quinidine.

A case control study found a 125-fold increased risk of severe thrombocytopenia (platelets <30,000 µL, requiring hospitalization) with quinidine.^2 The incidence of quinidine-induced thrombocytopenia was 1.8 cases per 1,000 patient years of exposure. The incidence of less severe thrombocytopenia may be higher.

Typically, a patient with immune thrombocytopenia will have taken drug for about 1 week or intermittently over a longer period of time (possibly years) before presenting with petechiae or bruising. Systemic symptoms, such as lightheadedness, chills, fever, nausea, and vomiting, often may precede bleeding events. Thrombocytopenia may be severe. Patients should have risk/benefit re-evaluated in order to continue treatment with quinidine. If the drug is stopped, symptoms usually resolve within 1 or 2 days and platelet count returns to normal in less than 1 week. If quinidine is not stopped, there is a risk of fatal hemorrhage. The onset of thrombocytopenia may be more rapid upon re-exposure.

PRECAUTIONS

Heart block

In patients without implanted pacemakers who are at high risk of complete atrioventricular block (e.g., those with digitalis intoxication, second degree atrioventricular block, or severe intraventricular conduction defects), quinidine should be used only with caution.

Thrombocytopenia

Quinidine should be discontinued in case of any signs or symptoms of thrombocytopenia (see WARNINGS).

Drug and Diet Interactions

Altered pharmacokinetics of quinidine: Diltiazem significantly decreases the clearance and increases the t1/2 of quinidine, but quinidine does not alter the kinetics of diltiazem.

Drugs that alkalinize the urine (carbonic-anhydrase inhibitors, sodium bicarbonate, thiazide diuretics) reduce renal elimination of quinidine.

By pharmacokinetic mechanisms that are not well understood, quinidine levels are increased by coadministration of amiodarone or cimetidine. Very rarely, and again by mechanisms not understood, quinidine levels are decreased by coadministration of nifedipine.

Hepatic elimination of quinidine may be accelerated by coadministration of drugs (phenobarbital, phenytoin, rifampin) that induce production of cytochrome P450IIIA4.

Perhaps because of competition for the P450IIIA4 metabolic pathway, quinidine levels rise when ketoconazole is coadministered.

Coadministration of propranolol usually does not affect quinidine pharmacokinetics, but in some studies the β-blocker appeared to cause increases in the peak serum levels of quinidine, decreases in quinidine's volume of distribution, and decreases in total quinidine clearance. The effects (if any) of coadministration of other β-blockers on quinidine pharmacokinetics have not been adequately studied.

Hepatic clearance of quinidine is significantly reduced during coadministration of verapamil, with corresponding increases in serum levels and half-life.

Grapefruit juice: Grapefruit juice inhibits P450 3A4-mediated metabolism of quinidine to 3-hydroxyquinidine. Although the clinical significance of this interaction is unknown, grapefruit juice should be avoided.

Dietary salt: The rate and extent of quinidine absorption may be affected by changes in dietary salt intake; a decrease in dietary salt intake may lead to an increase in plasma quinidine concentrations.

Altered pharmacokinetics of other drugs: Quinidine slows the elimination of digoxin and simultaneously reduces digoxin's apparent volume of distribution. As a result, serum digoxin levels may be as much as doubled. When quinidine and digoxin are coadministered, digoxin doses usually need to be reduced. Serum levels of digitoxin are also raised when quinidine is coadministered, although the effect appears to be smaller.

By a mechanism that is not understood, quinidine potentiates the anticoagulatory action of warfarin, and the anticoagulant dosage may need to be reduced.

Cytochrome P450IID6 is an enzyme critical to the metabolism of many drugs, notably including mexiletine, some phenothiazines, and most polycyclic antidepressants. Constitutional deficiency of cytochrome P450IID6 is found in less than 1% of Orientals, in about 2% of American blacks, and in about 8% of American whites. Testing with debrisoquine is sometimes used to distinguish the P450IID6-deficient "poor metabolizers" from the majority-phenotype "extensive metabolizers".

When drugs whose metabolism is P450IID6-dependent are given to poor metabolizers, the serum levels achieved are higher, sometimes much higher, than the serum levels achieved when identical doses are given to extensive metabolizers. To obtain similar clinical benefit without toxicity, doses given to poor metabolizers may need to be greatly reduced. In the case of prodrugs whose actions are actually mediated by P450IID6-produced metabolites (for example, codeine and hydrocodone, whose analgesic and antitussive effects appear to be mediated by morphine and hydromorphone, respectively), it may not be possible to achieve the desired clinical benefits in poor metabolizers.

Quinidine is not metabolized by cytochrome P450IID6, but therapeutic serum levels of quinidine inhibit the action of cytochrome P450IID6, effectively converting extensive metabolizers into poor metabolizers. Caution must be exercised whenever quinidine is prescribed together with drugs metabolized by cytochrome P450IID6.

Perhaps by competing for pathways of renal clearance, coadministration of quinidine causes an increase in serum levels of procainamide.

Serum levels of haloperidol are increased when quinidine is coadministered.

Presumably because both drugs are metabolized by cytochrome P450IIIA4, coadministration of quinidine causes variable slowing of the metabolism of nifedipine. Interactions with other dihydropyridine calcium channel blockers have not been reported, but these agents (including felodipine, nicardipine, and nimodipine) are all dependent upon P450IIIA4 for metabolism, so similar interactions with quinidine should be anticipated.

Altered pharmacodynamics of other drugs: Quinidine's anticholinergic, vasodilating, and negative inotropic actions may be additive to those of other drugs with these effects, and antagonistic to those of drugs with cholinergic, vasoconstricting, and positive inotropic effects. For example, when quinidine and verapamil are coadministered in doses that are each well tolerated as monotherapy, hypotension attributable to additive peripheral α-blockade is sometimes reported.

Quinidine potentiates the actions of depolarizing (succinylcholine, decamethonium) and non-depolarizing (d-tubocurarine, pancuronium) neuromuscular blocking agents. These phenomena are not well understood, but they are observed in animal models as well as in humans. In addition, in vitro addition of quinidine to the serum of pregnant women reduces the activity of pseudo-cholinesterase, an enzyme that is essential to the metabolism of succinylcholine.

Non-interactions of quinidine with other drugs: Quinidine has no clinically significant effect on the pharmacokinetics of diltiazem, flecainide, mephenytoin, metoprolol, propafenone, propranolol, quinine, timolol, or tocainide.

Conversely, the pharmacokinetics of quinidine are not significantly affected by caffeine, ciprofloxacin, digoxin, felodipine, omeprazole, or quinine. Quinidine's pharmacokinetics are also unaffected by cigarette smoking.

INFORMATION FOR PATIENTS

Before prescribing quinidine gluconate as prophylaxis against recurrence of atrial fibrillation, the physician should inform the patient of the risks and benefits to be expected (see CLINICAL PHARMACOLOGY). Discussion should include the facts:

- that the goal of therapy will be a reduction (probably not to zero) in the frequency of episodes of atrial fibrillation; and
- that reduced frequency of fibrillatory episodes may be expected, if achieved, to bring symptomatic benefit; but
- that no data are available to show that reduced frequency of fibrillatory episodes will reduce the risks of irreversible harm through stroke or death; and in fact
- that such data as are available suggest that treatment with quinidine gluconate is likely to increase the patient's risk of death.

Carcinogenesis, mutagenesis, impairment of fertility

Animal studies to evaluate quinidine's carcinogenic or mutagenic potential have not been performed. Similarly, there are no animal data as to quinidine's potential to impair fertility.

Pregnancy

TERATOGENIC EFFECTS

Pregnancy Category C. Animal reproductive studies have not been conducted with quinidine. There are no adequate and well-controlled studies in pregnant women. Quinidine should be given to a pregnant woman only if clearly needed.

In one neonate whose mother had received quinidine throughout her pregnancy, the serum level of quinidine was equal to that of the mother, with no apparent ill effect. The level of quinidine in amniotic fluid was about three times higher than that found in serum.

Labor and Delivery

Quinine is said to be oxytocic in humans, but there are no adequate data as to quinidine's effects (if any) on human labor and delivery.

Nursing mothers

Quinidine is present in human milk at levels slightly lower than those in maternal serum; a human infant ingesting such milk should (scaling directly by weight) be expected to develop serum quinidine levels at least an order of magnitude lower than those of the mother. On the other hand, the pharmacokinetics and pharmacodynamics of quinidine in human infants have not been adequately studied, and neonates' reduced protein binding of quinidine may increase their risk of toxicity at low total serum levels. Administration of quinidine should (if possible) be avoided in lactating women who continue to nurse.

Geriatric use

Safety and efficacy of quinidine in elderly patients have not been systematically studied.

Pediatric use

In antimalarial trials, quinidine was as safe and effective in pediatric patients as in adults. Notwithstanding the known pharmacokinetic differences between children and adults (see Pharmacokinetics and Metabolism), children in these trials received the same doses (on a mg/kg basis) as adults.

Safety and effectiveness of antiarrhythmic use in children have not been established.

ADVERSE REACTIONS

Quinidine preparations have been used for many years, but there are only sparse data from which to estimate the incidence of various adverse reactions. The adverse reactions most frequently reported have consistently been gastrointestinal, including diarrhea, nausea, vomiting, and heartburn/esophagitis.

In the reported study that was closest in character to the predominant approved use of quinidine gluconate, 86 adult outpatients with atrial fibrillation were followed for six months while they received slow-release quinidine bisulfate tablets, 600 mg (approximately 400 mg of quinidine base) twice daily. The incidences of adverse experiences reported more than once were as shown in the table below. The most serious quinidine-associated adverse reactions are described above under WARNINGS.

ADVERSE EXPERIENCES REPORTED MORE THAN ONCE IN 86 PATIENTS WITH ATRIAL FIBRILLATION
 | Incidence | (%)
diarrhea | 21 | (24%)
fever | 5 | (6%)
rash | 5 | (6%)
arrhythmia | 3 | (3%)
abnormal electrocardiogram | 3 | (3%)
nausea/vomiting | 3 | (3%)
dizziness | 3 | (3%)
headache | 3 | (3%)
asthenia | 2 | (2%)
cerebral ischemia | 2 | (2%)

Vomiting and diarrhea can occur as isolated reactions to therapeutic levels of quinidine, but they may also be the first signs of cinchonism, a syndrome that may also include tinnitus, reversible high-frequency hearing loss, deafness, vertigo, blurred vision, diplopia, photophobia, headache, confusion, and delirium. Cinchonism is most often a sign of chronic quinidine toxicity, but it may appear in sensitive patients after a single moderate dose.

A few cases of hepatotoxicity, including granulomatous hepatitis, have been reported in patients receiving quinidine. All of these have appeared during the first few weeks of therapy, and most (not all) have remitted once quinidine was withdrawn.

Autoimmune and inflammatory syndromes associated with quinidine therapy have included fever, urticaria, flushing, exfoliative rash, bronchospasm, psoriasiform rash, pruritus and lymphadenopathy, hemolytic anemia, vasculitis, thrombocytopenia, thrombocytopenic purpura, uveitis, angioedema, agranulocytosis, the sicca syndrome, arthralgia, myalgia, elevation in serum levels of skeletal-muscle enzymes, a disorder resembling systemic lupus erythematosus, and pneumonitis.

Convulsions, apprehension, and ataxia have been reported, but it is not clear that these were not simply the results of hypotension and consequent cerebral hypoperfusion. There are many reports of syncope. Acute psychotic reactions have been reported to follow the first dose of quinidine, but these reactions appear to be extremely rare.

Other adverse reactions occasionally reported include depression, mydriasis, disturbed color perception, night blindness, scotomata, optic neuritis, visual field loss, photosensitivity, and abnormalities of pigmentation.

OVERDOSAGE

Overdoses with various oral formulations of quinidine have been well described. Death has been described after a 5-gram ingestion by a toddler, while an adolescent was reported to survive after ingesting 8 grams of quinidine.

The most important ill effects of acute quinidine overdoses are ventricular arrhythmias and hypotension. Other signs and symptoms of overdose may include vomiting, diarrhea, tinnitus, high-frequency hearing loss, vertigo, blurred vision, diplopia, photophobia, headache, confusion and delirium.

Arrhythmias

Serum quinidine levels can be conveniently assayed and monitored, but the electrocardiographic QTc interval is a better predictor of quinidine-induced ventricular arrhythmias.

The necessary treatment of hemodynamically unstable polymorphic ventricular tachycardia (including torsades de pointes) is withdrawal of treatment with quinidine and either immediate cardioversion or, if a cardiac pacemaker is in place or immediately available, immediate overdrive pacing. After pacing or cardioversion, further management must be guided by the length of the QTc interval.

Quinidine-associated ventricular tachyarrhythmias with normal underlying QTc intervals have not been adequately studied. Because of the theoretical possibility of QT-prolonging effects that might be additive to those of quinidine, other antiarrhythmics with Class I (disopyramide, procainamide) or Class III activities should (if possible) be avoided. Similarly, although the use of bretylium in quinidine overdose has not been reported, it is reasonable to expect that the α-blocking properties of bretylium might be additive to those of quinidine, resulting in problematic hypotension.

If the post-cardioversion QTc interval is prolonged, then the pre-cardioversion polymorphic ventricular tachycardia was (by definition) torsades de pointes. In this case, lidocaine and bretylium are unlikely to be of value, and other Class I antiarrhythmics (disopyramide, procainamide) are likely to exacerbate the situation. Factors contributing to QTc prolongation (especially hypokalemia and hypomagnesemia) should be sought out and (if possible) aggressively corrected. Prevention of recurrent torsades may require sustained overdrive pacing or the cautious administration of isoproterenol (30 to 150 ng/kg/min).

Hypotension

Quinidine-induced hypotension that is not due to an arrhythmia is likely to be a consequence of quinidine-related α-blockade and vasorelaxation. Simple repletion of central volume (Trendelenburg positioning, saline infusion) may be sufficient therapy; other interventions reported to have been beneficial in this setting are those that increase peripheral vascular resistance, including α-agonist catecholamines (norepinephrine, metaraminol) and the Military Anti-Shock Trousers.

Treatment

To obtain up-to-date information about the treatment of overdose, a good resource is your certified Regional Poison-Control Center. Telephone numbers of certified poison-control centers are listed in the Physicians' Desk Reference (PDR). In managing overdose, consider the possibilities of multiple-drug overdoses, drug-drug interactions, and unusual drug kinetics in your patient.

Accelerated removal

Adequate studies of orally-administered activated charcoal in human overdoses of quinidine have not been reported, but there are animal data showing significant enhancement of systemic elimination following this intervention, and there is at least one human case report in which the elimination half-life of quinidine in the serum was apparently shortened by repeated gastric lavage. Activated charcoal should be avoided if an ileus is present; the conventional dose is 1 gram/kg administered every 2 to 6 hours as a slurry with 8 mL/kg of tap water.

Although renal elimination of quinidine might theoretically be accelerated by maneuvers to acidify the urine, such maneuvers are potentially hazardous and of no demonstrated benefit.

Quinidine is not usefully removed from the circulation by dialysis.

Following quinidine overdose, drugs that delay elimination of quinidine (cimetidine, carbonic-anhydrase inhibitors, diltiazem, thiazide diuretics) should be withdrawn unless absolutely required.

DOSAGE AND ADMINISTRATION

The dose of quinidine delivered by quinidine gluconate extended-release tablets may be titrated by breaking a tablet in half. If tablets are crushed or chewed, their extended-release properties will be lost.

The dosage of quinidine varies considerably depending upon the general condition and the cardiovascular state of the patient.

Conversion of atrial fibrillation/flutter to sinus rhythm

Especially in patients with known structural heart disease or other risk factors for toxicity, initiation or dose-adjustment of treatment with quinidine gluconate should generally be performed in a setting where facilities and personnel for monitoring and resuscitation are continuously available. Patients with symptomatic atrial fibrillation/flutter should be treated with quinidine gluconate only after ventricular rate control (e.g., with digitalis or β-blockers) has failed to provide satisfactory control of symptoms.

Adequate trials have not identified an optimal regimen of quinidine gluconate for conversion of atrial fibrillation/flutter to sinus rhythm. In one reported regimen, the patient first receives two tablets (648 mg; 403 mg of quinidine base) of quinidine gluconate every eight hours. If this regimen has not resulted in conversion after 3 or 4 doses, then the dose is cautiously increased. If, at any point during administration, the QRS complex widens to 130% of its pre-treatment duration; the QTc interval widens to 130% of its pre-treatment duration and is then longer than 500 ms; P waves disappear; or the patient develops significant tachycardia, symptomatic bradycardia, or hypotension, then quinidine gluconate is discontinued, and other means of conversion (e.g., direct-current cardioversion) are considered.

In another regimen sometimes used, the patient receives one tablet (324 mg; 202 mg of quinidine base) every eight hours for two days; then two tablets every twelve hours for two days; and finally two tablets every eight hours for up to four days. The four-day stretch may come at one of the lower doses if, in the judgment of the physician, the lower dose is the highest one that will be tolerated. The criteria for discontinuation of treatment with quinidine gluconate are the same as in the other regimen.

Reduction in the frequency of relapse into atrial fibrillation/flutter

In a patient with a history of frequent symptomatic episodes of atrial fibrillation/flutter, the goal of therapy with quinidine gluconate should be an increase in the average time between episodes. In most patients, the tachyarrhythmia will recur during therapy with quinidine gluconate, and a single recurrence should not be interpreted as therapeutic failure.

Especially in patients with known structural heart disease or other risk factors for toxicity, initiation or dose-adjustment of treatment with quinidine gluconate should generally be performed in a setting where facilities and personnel for monitoring and resuscitation are continuously available. Monitoring should be continued for two or three days after initiation of the regimen on which the patient will be discharged.

Therapy with quinidine gluconate should be begun with one tablet (324 mg; 202 mg of quinidine base) every eight or twelve hours. If this regimen is well tolerated, if the serum quinidine level is still well within the laboratory's therapeutic range, and if the average time between arrhythmic episodes has not been satisfactorily increased, then the dose may be cautiously raised. The total daily dosage should be reduced if the QRS complex widens to 130% of its pre-treatment duration; the QTc interval widens to 130% of its pre-treatment duration and is then longer than 500 ms; P waves disappear; or the patient develops significant tachycardia, symptomatic bradycardia, or hypotension.

Suppression of life-threatening ventricular arrhythmias

Dosing regimens for the use of quinidine gluconate in suppressing life-threatening ventricular arrhythmias have not been adequately studied. Described regimens have generally been similar to the regimen described just above for the prophylaxis of symptomatic atrial fibrillation/flutter. Where possible, therapy should be guided by the results of programmed electrical stimulation and/or Holter monitoring with exercise.

HOW SUPPLIED

Quinidine gluconate extended-release tablets, 324 mg are white to off-white, round, unscored, debossed MP 66.

Bottles of 100 | NDC 51407-288-01

STORAGE AND HANDLING

Store at 20° to 25°C (68° to 77°F).

[See USP Controlled Room Temperature]

DISPENSE IN TIGHT, LIGHT-RESISTANT CONTAINER.

References:

1. Aster RH, Curtis BR, McFarland JG, Bougie DW. Drug-induced immune thrombocytopenia: pathogenesis, diagnosis, and management. J Thromb Haemost 2009; 7: 911–8.
2. Kaufman DW, Kelly JP, Johannes CB, Sandler A, Harmon D, Stolley PD, Shapiro S. Acute thrombocytopenic purpura in relation to the use of drugs. Blood 1993; 82: 2714–18.

Distributed by: Sun Pharmaceutical Industries, Inc.
Cranbury, NJ 08512

Rev 02, November 2014

Marketed by:
GSMS, Inc.
Camarillo, CA 93012 USA

PRINCIPAL DISPLAY PANEL - 324 mg Tablet Bottle Label

Quinidine Gluconate 324mg ER Tablets 100

NDC 51407-288-01